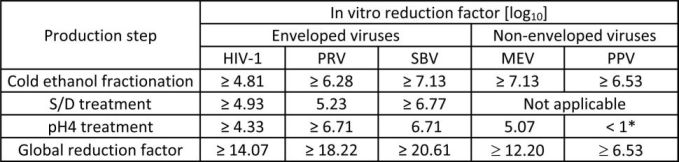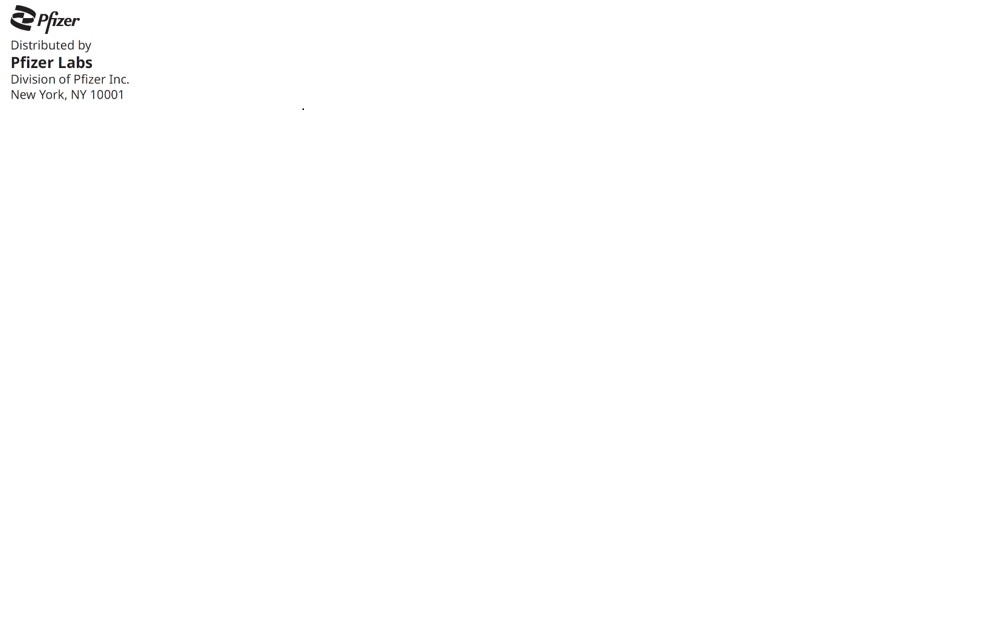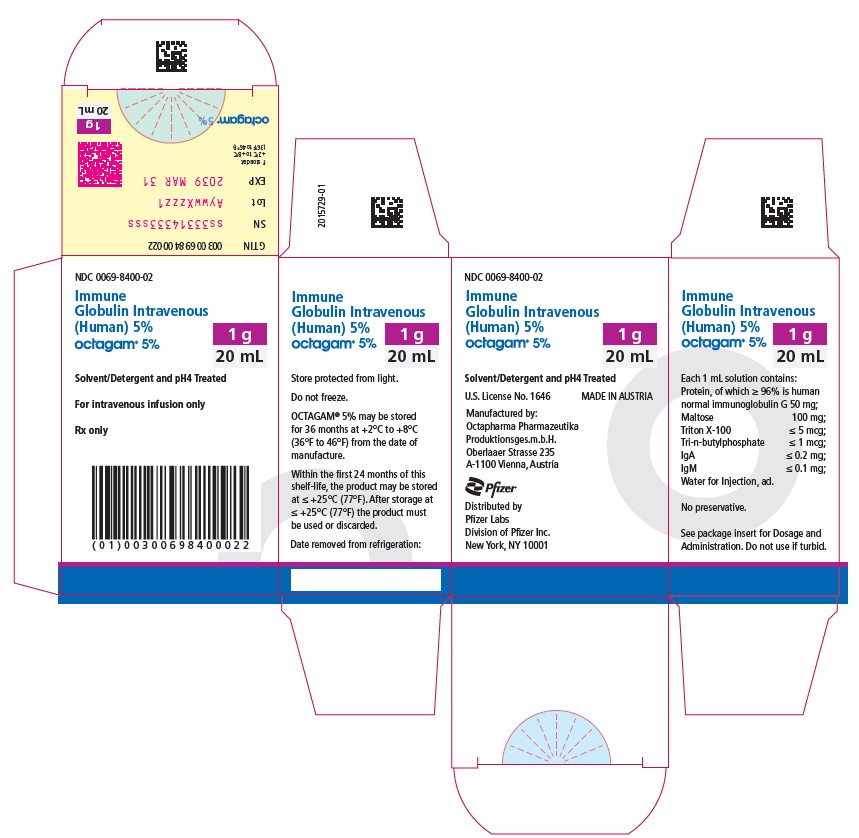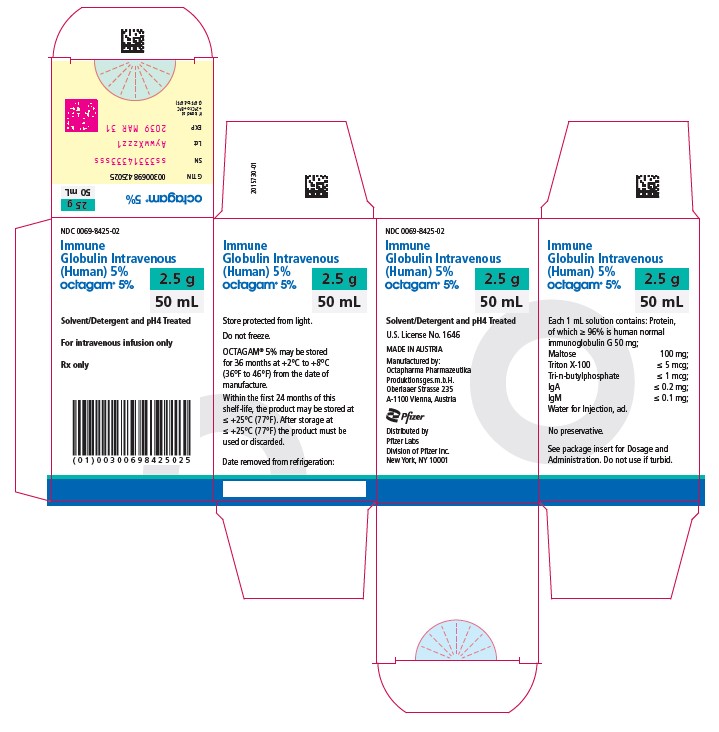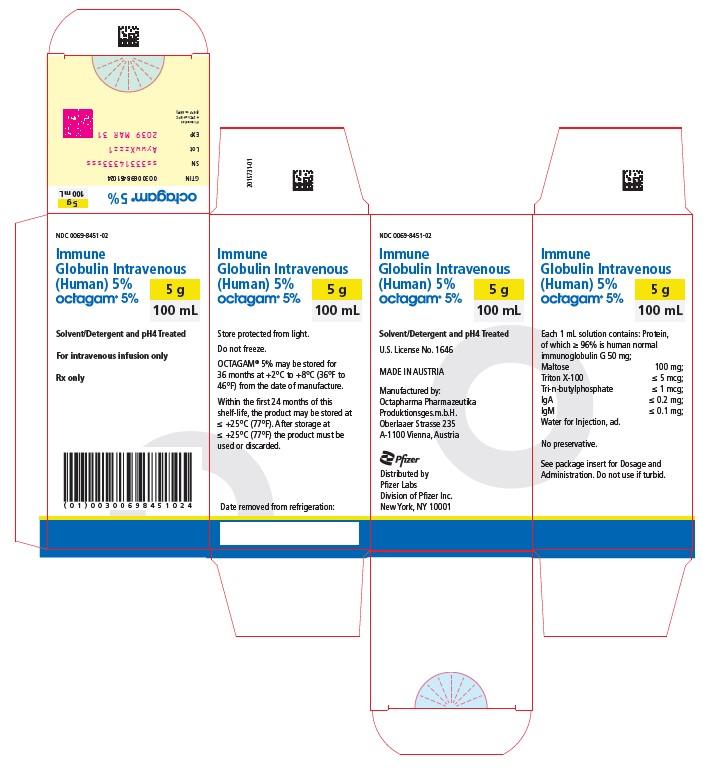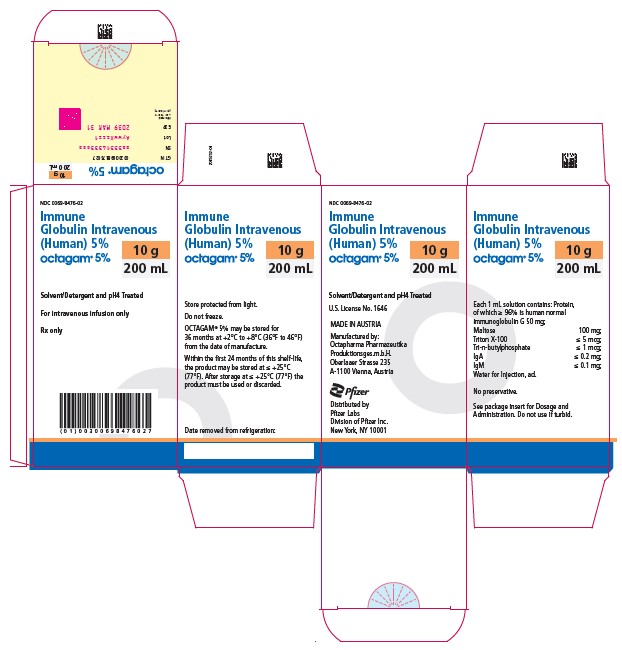 DRUG LABEL: Octagam Immune Globulin (Human)
NDC: 0069-8476 | Form: SOLUTION
Manufacturer: Pfizer Laboratories Div Pfizer Inc
Category: other | Type: PLASMA DERIVATIVE
Date: 20240129

ACTIVE INGREDIENTS: HUMAN IMMUNOGLOBULIN G 50 mg/1 mL

HIGHLIGHTS OF PRESCRIBING INFORMATION

These highlights do not include all the information needed to use Octagam, Immune Globulin Intravenous (Human), safely and effectively. See full prescribing information for Octagam.
Octagam [Immune Globulin Intravenous (Human)]
5% Liquid Preparation
Initial U.S. Approval: 2004

WARNING

WARNING: THROMBOSIS, RENAL DYSFUNCTION and ACUTE RENAL FAILURE

See full prescribing information for complete boxed warning.

Thrombosis may occur with immune globulin intravenous (IGIV) products, including Octagam 5% liquid. Risk factors may include: advanced age, prolonged immobilization, hypercoagulable conditions, history of venous or arterial thrombosis, use of estrogens, indwelling vascular catheters, hyperviscosity, and cardiovascular risk factors.

Renal dysfunction, acute renal failure, osmotic nephrosis, and death may occur in predisposed patients with IGIV products, including Octagam 5% liquid. Renal dysfunction and acute renal failure occur more commonly with IGIV products containing sucrose. Octagam 5% liquid does not contain sucrose.

For patients at risk of thrombosis, renal dysfunction or acute renal failure administer Octagam 5% liquid at the minimum dose and infusion rate practicable. Ensure adequate hydration in patients before administration. Monitor for signs and symptoms of thrombosis and assess blood viscosity in patients at risk for hyperviscosity.

1 INDICATIONS AND USAGE

Octagam is an immune globulin intravenous (human), 5% liquid, indicated for treatment of primary humoral immunodeficiency (PI) (1).

2 DOSAGE AND ADMINISTRATION

Intravenous use only (2).

Indication | Dose | Initial Infusion rate | Maintenance infusion rate (if tolerated)
PI | 300-600 mg/kgEvery 3-4 weeks | 0.5 mg/kg/min | 3.33 mg/kg/min

Ensure that patients with pre-existing renal insufficiency are not volume depleted; discontinue Octagam 5% liquid if renal function deteriorates (2.3).

For patients at risk of renal dysfunction or thrombotic events, administer Octagam 5% liquid at the minimum infusion rate practicable (2.3).

3 DOSAGE FORMS AND STRENGTHS

Octagam 5% liquid is supplied in 1.0 g, 2.5 g, 5 g, 10 g, or 25 g single use bottles (3 , 16).

4 CONTRAINDICATIONS

Anaphylactic or severe systemic reactions to human immunoglobulin (4)

IgA deficient patients with antibodies against IgA and a history of hypersensitivity (4)

Patients with acute hypersensitivity reaction to corn (4)

5 WARNINGS AND PRECAUTIONS

IgA deficient patients with antibodies against IgA are at greater risk of developing severe hypersensitivity and anaphylactic reactions. Epinephrine should be available immediately to treat any acute severe hypersensitivity reactions. (5.1)

Monitor renal function, including blood urea nitrogen and serum creatinine, and urine output in patients at risk of developing acute renal failure. (5.2)

Falsely elevated blood glucose readings may occur during and after the infusion of Octagam 5% liquid with some glucometer and test strip systems. (5.3)

Hyperproteinemia, increased serum viscosity and hyponatremia occur in patients receiving IGIV therapy. (5.4)

Thrombosis may occur following treatment with immune globulin products, including Octagam 5% liquid. Monitor for signs and symptoms of thrombosis and assess blood viscosity in patients at risk for hyperviscosity. (5.5)

Aseptic Meningitis Syndrome has been reported with Octagam 5% liquid and other IGIV treatments, especially with high doses or rapid infusion. (5.6)

Hemolytic anemia can develop subsequent to IGIV therapy due to enhanced RBC sequestration. (5.7)

IGIV recipients should be monitored for pulmonary adverse reactions (TRALI). (5.8)

The product is made from human plasma and may contain infectious agents, e.g. viruses and, theoretically, the Creutzfeldt-Jakob disease agent. (5.9)

The passive transfer of antibodies may confound the results of serological testing (5.11).

6 ADVERSE REACTIONS

Most common adverse reactions with an incidence of > 5% during a clinical trial were headache and nausea. (6). To report SUSPECTED ADVERSE REACTIONS, contact Pfizer Inc. at 1-800-438-1985 or FDA at 1-800-FDA-1088 or www.fda.gov/medwatch.

7 DRUG INTERACTIONS

The passive transfer of antibodies may interfere with the response to live viral vaccines (7).

8 USE IN SPECIFIC POPULATIONS

In patients over age 65 or in any person at risk of developing renal insufficiency, do not exceed the recommended dose, and infuse Octagam 5% liquid at the minimum infusion rate practicable (8.5).

_______________________________________________________________________________________________________________________________________

FULL PRESCRIBING INFORMATION

Octagam

Immune Globulin Intravenous (Human),

5% Liquid Preparation

WARNING

THROMBOSIS, RENAL DYSFUNCTION AND ACUTE RENAL FAILURE

Thrombosis may occur with immune globulin intravenous (IGIV) products, including Octagam 5% liquid. Risk factors may include: advanced age, prolonged immobilization, hypercoagulable conditions, history of venous or arterial thrombosis, use of estrogens, indwelling central vascular catheters, hyperviscosity, and cardiovascular risk factors. Thrombosis may occur in the absence of known risk factors. (See WARNING and PRECAUTIONS [ 5.5 ], PATIENT COUNSELING INFORMATION [ 17 ])

Renal dysfunction, acute renal failure, osmotic nephrosis, and death may occur in predisposed patients who receive IGIV products, including Octagam 5% liquid. Patients predisposed to renal dysfunction include those with a degree of pre-existing renal insufficiency, diabetes mellitus, age greater than 65, volume depletion, sepsis, paraproteinemia, or patients receiving known nephrotoxic drugs. Renal dysfunction and acute renal failure occur more commonly in patients receiving IGIV product containing sucrose. Octagam 5% liquid does not contain sucrose.

For patients at risk of thrombosis, renal dysfunction or acute renal failure, administer Octagam 5% liquid at the minimum dose and infusion rate practicable. Ensure adequate hydration in patients before administration. Monitor for signs and symptoms of thrombosis and assess blood viscosity in patients at risk for hyperviscosity. (See DOSAGE and ADMINISTRATION [ 2 ], WARNINGS and PRECAUTIONS [ 5.5 ])

1 INDICATIONS AND USAGE

Primary Humoral Immunodeficiency Diseases (PI)

Octagam is an immune globulin intravenous (human) 5% liquid indicated for treatment of primary humoral immunodeficiency (PI), such as congenital agammaglobulinemia, common variable immunodeficiency, X-linked agammaglobulinemia, Wiskott-Aldrich syndrome and severe combined immunodeficiencies.

2 DOSAGE AND ADMINISTRATION

For intravenous use only

2.1 Dose

As there are significant differences in the half-life of IgG among patients with primary humoral immunodeficiencies, the frequency and amount of immunoglobulin therapy may vary from patient to patient. The proper amount can be determined by monitoring clinical response.

The dose of Octagam 5% liquid for replacement therapy in primary humoral immunodeficiency diseases is 300 to 600 mg/kg body weight (6-12 mL/kg) administered every 3 to 4 weeks. Adjust the dosage over time to achieve the desired trough levels and clinical responses. If a patient on regular treatment missed a dose, administer the missed dose as soon as possible, and then continue treatment as before.

Measles Exposure

If a patient with primary humoral immunodeficiency has been exposed to measles, it may be prudent to administer an extra dose of IGIV as soon as possible and within 6 days of exposure. A dose of 400 mg/kg should provide a serum level > 240 mIU/mL of measles antibodies for at least two weeks.

If a patient with primary humoral immunodeficiency is at risk of future measles exposure and receives a dose of less than 530 mg/kg every 3-4 weeks, the dose should be increased to at least 530 mg/kg. This should provide a serum level of 240 mIU/mL of measles antibodies for at least 22 days after infusion.

2.2 Preparation

- Inspect each vial of Octagam 5% liquid visually for particulate matter and discoloration prior to administration, whenever solution and container permit. Do not use if the solution is turbid and/or a discoloration is observed.
- Do not freeze. Do not use solutions that have been frozen.
- Octagam 5% liquid contains no preservative. The Octagam 5% liquid bottle is for single use only. Promptly use any bottle that has been entered.
- Prior to use, allow the solution to reach ambient room temperature.
- Do not use after expiration date.
- The content of Octagam 5% liquid bottles may be pooled under aseptic conditions into sterile infusion bags and infused within 8 hours after pooling.
- Do not dilute Octagam 5% liquid. Do not mix Octagam 5% liquid with other medicinal products.
- Do not mix with immune globulin intravenous (IGIV) products from other manufacturers.

2.3 Administration

Octagam 5% liquid is for intravenous use only.

- The infusion line may be flushed before and after administration of Octagam 5% liquid with either normal saline or 5% dextrose in water.
- Administer Octagam 5% liquid at room temperature.
- Do not administer Octagam 5% liquid simultaneously with other intravenous preparations in the same infusion set.
- Octagam 5% liquid is not supplied with an infusion set. If using an in-line filter, choose a filter with a pore size of 0.2 – 200 microns.
- Do not use a needle of larger than 16 gauge to prevent the possibility of coring. Insert needle only once within the stopper area delineated (by the raised ring for penetration). Penetrate the stopper within the ring and perpendicularly to the plane of the stopper.
- Monitor the patient carefully throughout the infusion. Certain adverse drug reactions may be related to the rate of infusion. Slowing or stopping the infusion usually allows the symptoms to [subside or] disappear promptly. Once the symptoms subside, the infusion may then be resumed at a lower rate.
- Ensure that patients with pre-existing renal insufficiency are not volume depleted. For patients at risk of renal dysfunction or thromboembolic events, administer Octagam 5% at the minimum infusion rate practicable, not to exceed 3.3mg/kg/min (0.07 mL/kg/min). Discontinue Octagam 5% if renal function deteriorates.

Rate of Administration

Initially infuse Octagam 5% liquid at infusion rates stated below, at least until the physician has had adequate experience with a given patient.

Infusion rates (see also Table 1): 0.5 mg/kg/min (30 mg/kg/hr) for the first 30 minutes; if tolerated, advance to 1 mg/kg/min (60 mg/kg/hr) for the second 30 minutes; and if still tolerated, advance to 2 mg/kg/min (120 mg/kg/hr) for the third 30 minutes. If tolerated the infusion rate can be increased to and maintained at a maximum rate of 3.33 mg/kg/min (200 mg/kg/hr)

For patients judged to be at risk for developing renal dysfunction, administer Octagam 5% liquid at the minimum infusion rate practicable, not to exceed 0.07 mL/kg (3.3 mg/kg)/min (200 mg/kg/hr).

Table 1: Infusion Rates

Rate of Administration | mg/kg/min (mg/kg/hr) | mL/kg/min
first 30 min | 0.5 (30) | 0.01
next 30 min | 1.0 (60) | 0.02
next 30 min | 2.0 (120) | 0.04
Maximum | < 3.33 (< 200) | less than 0.07

- Certain severe adverse drug reactions may be related to the rate of infusion. Slowing or stopping the infusion usually allows the symptoms to disappear promptly.
- Ensure that patients with pre-existing renal insufficiency are not volume depleted; discontinue Octagam 5% liquid if renal function deteriorates.
- For patients at risk of renal dysfunction or thromboembolic events, administer Octagam 5% liquid at the minimum infusion rate practicable.

3 DOSAGE FORMS AND STRENGTHS

Octagam 5% liquid is supplied in 1.0 g, 2.5 g, 5 g, 10 g, or 25 g single use bottles (See How Supplied/Storage and Handling [ 16 ]).

4 CONTRAINDICATIONS

Octagam 5% liquid is contraindicated

- in patients who have acute severe hypersensitivity reactions to human immunoglobulin.
- in IgA deficient patients with antibodies against IgA and history of hypersensitivity. Octagam 5% liquid contains trace amounts of IgA (not more than 0.2 mg/mL in a 5% solution). (See Description [ 11 ])
- in patients with acute hypersensitivity reaction to corn. Octagam 5% liquid contains maltose, a disaccharide sugar that is derived from corn. Patients known to have corn allergies should avoid using Octagam 5% liquid.

5 WARNINGS AND PRECAUTIONS

5.1 Hypersensitivity Reactions

Severe hypersensitivity reactions may occur [ 1 ] (See Contraindications [ 4 ]) . In case of hypersensitivity, discontinue Octagam 5% liquid infusion immediately and institute appropriate treatment. Always have medications such as epinephrine available for immediate treatment of acute severe hypersensitivity reactions.

IgA deficient patients with antibodies against IgA are at greater risk of developing severe hypersensitivity and anaphylactoid reactions when administered Octagam 5% liquid (See Contraindications [ 4 ]) .

Patients known to have corn allergies should avoid using Octagam 5% liquid (See Contraindications [ 4 ]).

5.2 Renal Failure

Renal dysfunction, acute renal failure, osmotic nephropathy, and death may occur upon use of IGIV products in predisposed patients.

Assure that patients are not volume depleted prior to the initiation of the infusion of Octagam 5% liquid.

Assess renal function, including a measurement of blood urea nitrogen (BUN)/serum creatinine, prior to the initial infusion of Octagam 5% liquid and again at appropriate intervals thereafter. It is particularly important to do periodic monitoring of renal function tests and urine output in patients judged to have a potential increased risk of developing acute renal failure. Consider discontinuation of the infusion if renal function deteriorates. (See Patient Counseling Information [ 17 ].)

For patients judged to be at risk for developing renal dysfunction and/or at risk of developing thrombotic events (such as those with diabetes mellitus or hypovolemia, those who are obese, those who use concomitant nephrotoxic medicinal products, or those who are over 65 years of age), administer Octagam 5% liquid at the minimum rate of infusion practicable (less than 0.07 mL/kg/min (3.3 mg/kg/min) (See Boxed Warning, and Dosage and Administration [ 2.3 ]).

5.3 Blood Glucose Monitoring

Some types of blood glucose testing systems (for example, those based on the glucose dehydrogenase pyrroloquinolinequinone (GDH-PQQ) or glucose-dye-oxidoreductase methods) falsely interpret the maltose contained in Octagam 5% liquid as glucose. This has resulted in falsely elevated glucose readings and, consequently, in the inappropriate administration of insulin, resulting in life-threatening hypoglycemia. Further, cases of true hypoglycemia may go untreated if the hypoglycemic state is masked by falsely elevated glucose readings. Therefore, always use a glucose-specific method for the measurement of blood glucose, when administering Octagam 5% liquid. Carefully review the product information of the blood glucose testing system, including that of the test strips, to determine if the system is appropriate for use with maltose-containing parenteral products. If any uncertainty exists, contact the manufacturer of the testing system to determine if the system is appropriate for use with maltose-containing parenteral products. [ 2 ]

5.4 Hyperproteinemia

Hyperproteinemia, increased serum viscosity and hyponatremia may occur in patients receiving IGIV therapy, including Octagam 5% liquid. The hyponatremia is likely to be a pseudohyponatremia as demonstrated by a decreased calculated serum osmolality or elevated osmolar gap. Distinguishing true hyponatremia from pseudohyponatremia is clinically critical, as treatment aimed at decreasing serum free water in patients with pseudohyponatremia may lead to volume depletion, a further increase in serum viscosity and a disposition to thromboembolic events [ 3 ].

5.5 Thrombotic events

Thrombosis may occur following treatment with immune globulin products, including Octagam 5% liquid. Risk factors may include advanced age, prolonged immobilization, hypercoagulable conditions, history of venous or arterial thrombosis, use of estrogens, indwelling central vascular catheters, hyperviscosity, and cardiovascular risk factors. Thrombosis may occur in the absence of known risk factors.

Consider baseline assessment of blood viscosity in patients at risk for hyperviscosity, including those with cryoglobulins, fasting chylomicronemia/markedly high triacylglycerols (triglycerides), or monoclonal gammopathies. For patients at risk of thrombosis, administer Octagam 5% liquid at the minimum dose and infusion rate practicable. Ensure adequate hydration in patients before administration. Monitor for signs and symptoms of thrombosis and assess blood viscosity in patients at risk for hyperviscosity. [ 4 ], [ 5 ], [ 6 ]. (See Boxed Warning, Dosage and Administration [ 2 ], Patient Counseling Information [ 17 ])

5.6 Aseptic meningitis syndrome

Aseptic meningitis syndrome (AMS) has been reported to occur infrequently in association with IGIV treatment, including Octagam 5% liquid. Discontinuation of IGIV treatment has resulted in remission of AMS within several days without sequelae. The syndrome usually begins within several hours to two days following IGIV treatment and rapid infusion. It is characterized by symptoms and signs including severe headache, nuchal rigidity, drowsiness, fever, photophobia, painful eye movements, nausea and vomiting. Cerebrospinal fluid (CSF) studies are frequently positive with pleocytosis up to several thousand cells per cu mm, predominantly from the granulocytic series, and elevated protein levels up to several hundred mg/dl. Conduct a thorough neurological examination on patients exhibiting such signs and symptoms, including CSF studies, to rule out other causes of meningitis. AMS may occur more frequently in association with high doses (2 g/kg) and/or rapid infusion of IGIV. It appears that patients with a history of migraine may be more susceptible. [ 7 ] (See Patient Counseling Information [ 17 ]).

5.7 Hemolysis

Octagam 5% liquid may contain blood group antibodies, which may act as hemolysins and induce in vivo coating of red blood cells with immunoglobulin, causing a positive direct antiglobulin reaction and, rarely, hemolysis [ 8 ]. Delayed hemolytic anemia can develop subsequent to IGIV therapy due to enhanced RBC sequestration and acute hemolysis, consistent with intravascular hemolysis, has been reported. Cases of severe hemolysis-related renal dysfunction/failure or disseminated intravascular coagulation have occurred following infusion of IGIV (See Adverse Reactions [ 6 ]) [ 9 ].

The following risk factors may be associated with the development of hemolysis following IGIV administration: high doses (e.g. ≥ 2 g/kg), given either as a single administration or divided over several days, and non-O blood group. Other individual patient factors, such as an underlying inflammatory state (as may be reflected by, for example, elevated C-reactive protein or erythrocyte sedimentation rate), have been hypothesized to increase the risk of hemolysis following administration of IGIV but their role is uncertain. Hemolysis has been reported following administration of IGIV for a variety of indications.

Closely monitor patients for clinical signs and symptoms of hemolysis, particularly patients with risk factors noted above. Consider appropriate laboratory testing in higher risk patients, including measurement of hemoglobin or hematocrit prior to infusion and within approximately 36 to 96 hours post infusion. If clinical signs and symptoms of hemolysis or a significant drop in hemoglobin or hematocrit have been observed, perform confirmatory laboratory testing. If transfusion is indicated for patients who develop hemolysis with clinically compromising anemia after receiving IGIV, perform adequate cross-matching to avoid exacerbating on-going hemolysis. (See Patient Counseling Information [ 17 ]) .

5.8 Transfusion-Related Acute Lung Injury (TRALI)

Noncardiogenic pulmonary edema [Transfusion-Related Acute Lung Injury (TRALI)] may occur in patients treated with IGIV products, including Octagam 5% liquid [ 10 ]. TRALI is characterized by severe respiratory distress, pulmonary edema, hypoxemia, normal left ventricular function, and fever and typically occurs within 1-6 hours after transfusion.

Monitor patients for pulmonary adverse reactions (See Patient Counseling Information [ 17 ]) . If TRALI is suspected, perform appropriate tests for the presence of anti-neutrophil antibodies in both the product and patient serum. Patients with TRALI may be managed using oxygen therapy with adequate ventilatory support.

5.9 Transmissible Infectious Agents

Because Octagam 5% liquid is made from human blood, it may carry a risk of transmitting infectious agents, e.g., viruses and theoretically, the Creutzfeldt-Jakob disease (CJD) agent. The risk of infectious agent transmission has been reduced by screening plasma donors for prior exposure to certain viruses, testing for the presence of certain current virus infections, and including virus inactivation/removal steps in the manufacturing process for Octagam 5% liquid.

Report all infections thought to possibly be transmitted by Octagam 5% liquid to Pfizer Inc. at 1-800-438-1985 . Always discuss the risks and benefits of this product with the patient, before prescribing or administering it to the patient (See Patient Counseling Information [ 17 ]).

5.10 Laboratory Tests

- Periodic monitoring of renal function and urine output is particularly important in patients judged to be at increased risk of developing acute renal failure. Assess renal function, including measurement of BUN and serum creatinine, before the initial infusion of Octagam 5% liquid and at appropriate intervals thereafter.
- Consider baseline assessment of blood viscosity in patients at risk for hyperviscosity, including those with cryoglobulins, fasting chylomicronemia/markedly high triacylglycerols (triglycerides), or monoclonal gammopathies, because of the potentially increased risk of thrombosis.
- If signs and/or symptoms of hemolysis are present after an infusion of Octagam 5% liquid, perform appropriate laboratory testing for confirmation.
- If TRALI is suspected, perform appropriate tests for the presence of anti-neutrophil antibodies and anti-HLA antibodies in both the product and patient’s serum.

5.11 Interference with Laboratory Tests

After infusion of IgG, the transitory rise of the various passively transferred antibodies in the patient’s blood may yield positive serological testing results, with the potential for misleading interpretation. Passive transmission of antibodies to erythrocyte antigens (e.g., A, B, and D) may cause a positive direct or indirect antiglobulin (Coombs) test.

6 ADVERSE REACTIONS

The most common adverse reactions observed with Octagam 5% liquid treatment during clinical trial (> 5%) were headache and nausea.

The most serious adverse reactions observed with Octagam 5% liquid treatment have been immediate anaphylactic reactions (see Warning and Precautions [ 5.1 ]), thromboembolic events (Warning and Precautions [ 5.5 ]), aseptic meningitis (Warnings and Precautions [ 5.6 ]), and hemolytic anemia (Warnings and Precautions [ 5.7 ]).

6.1 Clinical Trials Experience

Because clinical trials are conducted under widely varying conditions, adverse reaction rates observed in the clinical trials of a product cannot be directly compared to rates in the clinical trials of another product and may not reflect the rates observed in clinical practice.

The clinical trial database includes a multi-center, study in 46 children and adults with PI. Subjects participated in the study for a mean of 346 days and received 300 to 450 mg/kg every 21 days or 400 to 600 mg/kg every 28 days. Infusions were initiated at a rate of 30 mg/kg/hr for the first 30 minutes, and, if tolerated, could be advanced to a maximum tolerated rate not exceeding 200 mg/kg/hr. Over half of the subjects were male (n=28; 61%), and more than half were on the 28-day infusion schedule (n=27; 59%). The mean age of subjects was 31.5 years.

Pre-medications were used in 165 (25.2%) out of 654 infusions and in 14 (30.4%) out of 46 patients. Infusions were slowed or interrupted in 9 out of 489 infusions (1.84%) without pre-medication and in 10 out of 165 infusions (6.06%) with pre-medication. Five out of 32 (15.63%) patients who never received any pre-medication had at least one slowed or interrupted infusion, whereas 9 out of 14 (64.29%) patients who received pre-medication at least once also had a slowed or interrupted infusion.

During the described trial 12 serious adverse events were reported in 6 patients. Eleven SAEs were assessed as being not related. One serious adverse event (Calculus renal NOS) war reported just before the next infusion, and was not temporarily related to the previous infusion. No subject withdrew from the study due to an adverse event or adverse reaction.

The adverse reactions (= adverse events that were assessed as treatment related) reported by at least 5% of subjects during the 12-month treatment are given in Table 2 below.

Table 2: Adverse Reactions Occurring in ≥ 5% of Subjects Receiving Octagam 5%

 | No. of subjects (%) | No. of events (%)
Total | 46 (100%) | 71 (100%)
Headache NOS | 7 (15%) | 18 (25%)
Nausea | 3 (7%) | 4 (6%)

Laboratory Abnormalities

Standard clinical laboratory evaluations were performed in the study. Three subjects (7%) had incidences of AST (>2.5 x ULN) which were all assessed as clinically non-significant. No subject had a positive Coombs test or other signs of hemolysis (such as drop of hemoglobin of ≥ 2 g/dL) during the study.

6.2 Postmarketing Experience

Because postmarketing reporting of adverse reactions is voluntary and from a population of uncertain size, it is not always possible to reliably estimate the frequency of these reactions or establish a causal relationship to product exposure.

The following adverse reactions have been identified during post-approval use of Octagam 5% liquid.

Blood and lymphatic system disorders
Leukopenia, hemolytic anemia

Immune system disorders
Hypersensitivity, anaphylactic shock, anaphylactic reaction, anaphylactoid reaction, angioedema, face oedema

Metabolic and nutritional disorders
Fluid overload, (pseudo)hyponatremia

Psychiatric disorders
Agitation, confusional state, anxiety, nervousness

Nervous system disorders
Cerebrovascular accident, loss of consciousness, speech disorder, meningitis aseptic, migraine, dizziness, paresthesia, hypoesthesia, tremor, photophobia

Eye disorders
Visual impairment

Cardiac disorders
Myocardial infarction, angina pectoris, bradycardia, tachycardia, palpitations, cyanosis

Vascular disorders
Hypotension, thrombosis, circulatory collapse, peripheral circulatory failure, hypertension, phlebitis, pallor

Respiratory, thoracic and mediastinal disorders
Respiratory failure, pulmonary embolism, pulmonary oedema, bronchospasm, dyspnea, cough, hypoxia

Gastrointestinal disorders
Vomiting, diarrhea, abdominal pain

Skin and subcutaneous tissue disorders
Eczema, skin exfoliation, urticaria, rash, rash erythematous, dermatitis, erythema, pruritus, alopecia

Musculoskeletal and connective tissue disorders
Back pain, arthralgia, myalgia, pain in extremity, neck pain, muscle spasm, muscular weakness, musculoskeletal stiffness

Renal and urinary disorders
Renal failure acute, renal pain

General disorders and administration site conditions
Fatigue, oedema, injection site reaction, pyrexia, influenza-like illness, chills, chest pain, chest discomfort, hot flush, flushing, feeling hot, feeling cold, hyperhidrosis, malaise, lethargy, asthenia, burning sensation

Investigations
Hepatic enzymes increased, blood glucose false positive

Injury, poisoning and procedural complications
Transfusion-related acute lung injury

7 DRUG INTERACTIONS

It is recommended that Octagam 5% liquid be administered separately from other drugs or medications which the patient may be receiving.

Antibodies in Octagam 5% liquid may interfere with the response to live viral vaccines, such as measles, mumps, and rubella. Inform the immunizing physician of recent therapy with Octagam 5% liquid, so that administration of live viral vaccines, if indicated, can be appropriately delayed 3 or more months from the time of IGIV administration .

8 USE IN SPECIFIC POPULATIONS

8.1 Pregnancy

Risk Summary

No human data are available to indicate the presence or absence of drug-associated risk. Animal reproduction studies have not been conducted with Octagam 5% liquid. It is not known whether Octagam 5% liquid can cause fetal harm when administered to a pregnant woman. Immune globulins cross the placenta from maternal circulation increasingly after 30 weeks of gestation. In the U.S. general population, the estimated background risk of major birth defects and miscarriage in clinically recognized pregnancies is 2-4% and 15-20%, respectively.

8.2 Lactation

Risk Summary

No human data are available to assess the presence or absence of Octagam 5% in human milk, the effects of Octagam 5% on the breastfed child, and the effects of Octagam 5% on milk production/excretion. The developmental and health benefits of breastfeeding should be considered along with the mother’s clinical need for Octagam 5% liquid and any potential adverse effects on the breastfed infant from Octagam 5% liquid or from the underlying maternal condition. Immunoglobulins are excreted into the milk and may contribute to the transfer of protective antibodies to the neonate.

8.4 Pediatric Use

Octagam 5% liquid was evaluated in 11 pediatric subjects (age range 6 – 16 years). There were no obvious differences observed between adults and pediatric subjects with respect to pharmacokinetics, efficacy and safety. No pediatric specific dose requirements were necessary to achieve the desired serum IgG levels.

8.5 Geriatric Use

Patients > 65 years of age may be at increased risk for developing certain adverse reactions such as thromboembolic events and acute renal failure (See Boxed Warning, Warnings and Precautions [ 5 ]).

Clinical studies of Octagam 5% liquid did not include sufficient numbers of subjects aged 65 and over to determine whether they respond differently from younger subjects. Other reported clinical experience has not identified differences in responses between the elderly and younger patients. In general, dose selection for an elderly patient should be cautious, usually starting at the low end of the dosing range, reflecting the greater frequency of decreased hepatic, renal, or cardiac function, and of concomitant disease or other drug therapy.

10 OVERDOSAGE

Overdose may lead to fluid overload and hyperviscosity, particularly in the elderly and in patients with impaired renal function.

11 DESCRIPTION

Immune Globulin Intravenous (Human), Octagam 5% liquid, is a solvent/detergent (S/D)-treated, sterile preparation of highly purified immunoglobulin G (IgG) derived from large pools of human plasma. Octagam 5% liquid is a solution for infusion which must be administered intravenously.

All units of human plasma used in the manufacture of Octagam 5% liquid are provided by FDA-approved blood establishments only, and are tested by FDA-licensed serological tests for HBsAg, antibodies to HCV and HIV and Nucleic Acid Test (NAT) for HCV and HIV-1 and found to be non-reactive (negative).

The product is manufactured by the cold ethanol fractionation process followed by ultrafiltration and chromatography. The manufacturing process includes treatment with an organic S/D mixture composed of tri-n-butyl phosphate (TNBP) and Triton X-100 (Octoxynol). The Octagam 5% liquid manufacturing process provides a significant viral reduction in in vitro studies (Table 3). These reductions are achieved through a combination of process steps including cold ethanol fractionation, S/D treatment and pH 4 treatment.

Table 3: In vitro reduction factor during Octagam 5% liquid manufacturing

*not calculated for global LRF

HIV-1: Human Immunodeficiency Virus - 1

PRV: Pseudorabies Virus

SBV: Sindbis Virus

MEV: Mouse Encephalomyelitis Virus

PPV: Porcine Parvovirus

11.1 Composition

The composition of Octagam 5% liquid is shown in Table 4 as follows:

Table 4: Composition.

Component | Quantity/mL
Protein, of which not less than 96% is human normal immunoglobulin G | 50 mg
Maltose | 100 mg
Triton X-100 | not more than 5 mcg
TNBP | not more than 1 mcg
IgA | not more than 0.2 mg
IgM | not more than 0.1 mg
Water for Injection | ad.

This preparation contains approximately 50 mg of protein per mL (5%) of which not less than 96% is human normal immunoglobulin G. Octagam 5% liquid contains not more than 3% aggregates, not less than 90% monomers and dimers and not more than 3% fragments.

The sodium content of the final solution is not more than 30 mmol/l and the pH is between 5.1 and 6.0. The osmolality is 310 - 380 mosmol/kg.

The manufacturing process for Octagam 5% liquid isolates IgG without additional chemical or enzymatic modification, and the Fc portion is maintained intact. Octagam 5% liquid contains the IgG antibody activities present in the donor population. IgG subclasses are fully represented with the following approximate percents of total IgG: IgG 1 is 65%, IgG 2 is 30%, IgG 3 is 3% and IgG 4 is 2%.

Octagam 5% liquid contains a broad spectrum of IgG antibodies against bacterial and viral agents that are capable of opsonization and neutralization of microbes and toxins.

Octagam 5% liquid contains no preservative and no sucrose.

12 CLINICAL PHARMACOLOGY

12.1 Mechanism of Action

Octagam 5% liquid supplies a broad spectrum of opsonic and neutralizing IgG antibodies against bacteria or their toxins. The mechanism of action in PI has not been fully elucidated.

12.2 Pharmacodynamics

Octagam 5% liquid contains mainly immunoglobulin G (IgG) with a broad spectrum of antibodies against various infectious agents reflecting the IgG activity found in the donor population. Octagam 5% liquid which is prepared from pooled material from not less than 1000 donors, has an IgG subclass distribution similar to that of native human plasma. Adequate doses of IGIV can restore abnormally low IgG level to the normal range. Standard pharmacodynamic studies were not performed.

12.3 Pharmacokinetics

Peak levels of IgG are reached immediately after infusion of Octagam 5% liquid . It has been shown that after infusion, exogenous IgG is distributed relatively rapidly between plasma and extravascular fluid until approximately half is partitioned in the extravascular space. Therefore a rapid initial drop in serum IgG is expected [ 11 ].

Studies show that the apparent half-life of Octagam 5% liquid is approximately 40 days in immunodeficient patients.

The main pharmacokinetic parameters of Octagam 5% liquid measured as total IgG in the clinical study are displayed in Table 5 below:

In the pharmacokinetic study, a subset of 14 patients aged between 10 and 70 years with PI underwent pharmacokinetic assessments. Patients received infusions of Octagam 5% liquid (300 to 600 mg/kg) every 3 (n=6) to 4 (n=8) weeks for 12 months. Pharmacokinetic samples were collected at baseline and after the 5 th month of treatment. After the infusion, blood samples were taken until day 28 (for patients on a 21 day schedule, the interval was extended to 4 weeks for the pharmacokinetic study).

Table 5: PK Parameters of Octagam 5% liquid in the clinical study

 |  | Octagam | 5% liquid
 | N | Mean | SD | Median
Cmax (mg/mL) | 14 | 16.7 | 3.2 | 16.4
AUC (mg*h/mL) | 14 | 7022 | 1179 | 7103
T1/2 (days) | 14 | 40.7 | 17.0 | 36.3
Trough IgG Level 21 Day Infusion Schedule (mg/dL) | 19 | 881.6 | 151.5 | 859
Trough IgG Level 28 Day Infusion Schedule (mg/dL) | 25 | 763.5 | 156.8 | 760

The half-life of IgG can vary considerably from person to person. In particular, high concentrations of IgG and hypermetabolism associated with fever and infection have been seen to coincide with a shortened half-life of IgG. Longer half-lives are often seen with immunodeficient patients [ 12 ].

13 NONCLINICAL TOXICOLOGY

13.1 Carcinogenesis, Mutagenesis, Impairment of Fertility

No studies were conducted on carcinogenesis, mutagenesis, or impairment of fertility with Octagam 5% liquid.

Repeated-dose toxicity studies and the genotoxic studies gave no evidence of carcinogenic properties of TNBP and Octoxynol [ 13 ], [ 14 ].

The results of in vitro and in vivo genotoxicity studies for TNBP and Octoxynol were negative. The results of studies on the embryotoxic and teratogenic properties of TNBP and Octoxynol in rats and rabbits at a wide range of i.v. doses were also negative.

13.2 Animal Toxicology and/or Pharmacology

No studies were conducted on non-clinical pharmacology, toxicology, local tolerance or pharmacokinetics with Octagam 5% liquid.

A variety of single-dose toxicity studies were performed for TNBP and Octoxynol alone or in combination. The lowest toxic dose of TNBP + Octoxynol (1+5) was 10,000 mcg/kg BM in rats after intravenous administration. Studies on 13-week toxicity were performed for combinations of TNBP + Octoxynol in a broad dose range intravenously in dogs and rats. In these studies the lowest toxic dose for rats was local 60 mcg TNBP/kg +300 mcg Octoxynol/kg BM i.v. (concentration: 0.0006% and 0.003%, respectively) and systemic 300 mcg TNBP/kg + 1,500 mcg Octoxynol/kg BM i.v. (concentration: 0.003% and 0.015%, respectively). The lowest toxic dose for dogs was local 50 mcg TNBP/kg + 250 mcg Octoxynol/kg BM i.v. (concentration: 0.005% and 0.025%, respectively) and systemic 500 mcg TNBP/kg + 2,500 mcg Octoxynol/kg BM i.v. (concentration: 0.05% and 0.25%, respectively).

Local tolerance of TNBP and Octoxynol was evaluated from the experiments on repeat-dose toxicity (rats, dogs) and on developmental toxicity (rats, rabbits). In these animal studies the lowest dose exerting local adverse reactions was 50 + 250 mcg/kg BM (TNBP + Octoxynol; daily injections) in dogs. At this dose 4 out of 6 dogs were affected starting in week 7 of treatment.

A pharmacokinetic study was carried out in rats given 300 mcg of TNBP/kg and 1,500 mcg Octoxynol/kg BM i.v. The plasma half-life for TNBP was approximately 20 minutes. Octoxynol was not detected.

14 CLINICAL STUDIES

In an open-label, multicenter study, 46 patients (including 10 patients between the ages of 6 and 12, and one 15 years old) with primary humoral immunodeficiency (PI) received Octagam 5% liquid in individualized doses of 300 - 600 mg/kg every 3 or 4 weeks for 12 months. More than half of the patients (n=27; 59%) were on a 4-week treatment schedule, the remainder received the study drug every 3 weeks. Six patients discontinued the study prematurely.

The study examined the number of episodes of serious infections (pneumonia, bacteremia, sepsis, osteomyelitis, septic arthritis, visceral abscesses, bacterial or viral meningitis) per patient in a year, as well as the number of other infections, number of school or work days missed, the number and length of hospitalizations, and the number of visits to a physician or the emergency department for acute problems.

The rate of serious infections per patient per year was 0.1 (5 infections over 43.5 patient-years). There were no other infections documented by positive radiograph or fever during the study period. Table 6 summarizes the other efficacy data such as work/school days missed, days in hospital and visits to physician/ER.

Table 6: Summary of Secondary Efficacy Variables.

Variable | Subjects N | Subjects % | Total Days or Visits | Total Subject Years | Days or Visits/Subj./YearEstimate
Work/School Days Missed | 30 | 65 | 241 | 43.5 | 5.5
Days in Hospital | 4 | 9 | 16 | 43.5 | 0.4
Visits to Physician/ER | 27 | 59 | 92 | 43.5 | 2.1

15 REFERENCES

1. Duhem, C., Dicato, M. A. and Ries, F. Side-effects of intravenous immune globulins. Clin. Exp. Immunol. 97 Suppl 1, 79-83 (1994).
2. Kannan, S., Rowland, C. H., Hockings, G. I. and Tauchmann, P. M. Intragam can interfere with blood glucose monitoring. Med. J. Aust. 180, 251-252 (2004).
3. Steinberger, B. A., Ford, S. M., Coleman, T. A. Intravenous Immunoglobulin Therapy Results in Post-infusional Hyperproteinemia, Increased Serum Viscosity, and Pseudohyponatremia. Am J Hematol 73:97-100 (2003)
4. Dalakas, M. C. High-dose intravenous immunoglobulin and serum viscosity: risk of precipitating thromboembolic events. Neurology 44, 223-226 (1994).
5. Wolberg, A. S., Kon, R. H., Monroe, D. M. and Hoffman, M. Coagulation factor XI is a contaminant in intravenous immunoglobulin preparations. Am. J Hematol. 65, 30-34 (2000).
6. Go RS, Call TG: Deep venous thrombosis of the arm after intravenous immunoglobulin infusion: case report and literature review of intravenous immunoglobulin-related thrombotic complications. Mayo Clin Proc75:83-85 (2000)
7. Sekul, E. A., Cupler, E. J. and Dalakas, M. C. Aseptic meningitis associated with high-dose intravenous immunoglobulin therapy: frequency and risk factors. Ann Intern. Med. 121, 259-262 (1994).
8. Pierce LR, Jain N: Risks associated with the use of intravenous immunoglobulin. Transfus Med Rev 17:241-251 (2003)
9. Kessary-Shoham H., Levy, Y., Shoenfeld, Y., Lorber, M. and Gershon, H. In vivo administration of intravenous immunoglobulin (IVIg) can lead to enhanced erythrocyte sequestration. Journal of Autoimmunity. 13, 129-135 (1999).
10. Rizk, A., Gorson, K. C., Kenney, L. and Weinstein, R. Transfusion-related acute lung injury after the infusion of IVIG. Transfusion 41, 264-268 (2001).
11. Koleba T, Ensom MH: Pharmacokinetics of intravenous immunoglobulin: a systematic review. Pharmacotherapy 26:813-827 (2006)
12. Lever, A. M., Yap, P. L., Cuthbertson, B., Wootton, R. and Webster, A. D. Increased half-life of gammaglobulin after prolonged intravenous replacement therapy. Clin Exp. Immunol 67, 441-446 (1987).
13. Auletta, CS., Kotkoskie, LA., Saulog, T., Richter, WR. A dietary oncogenicity study of tributyl phosphate in the CD-1 mouse. Toxicology 128, 135-141 (1998a).
14. Auletta CS., Weiner ML., Richter WR. A dietary toxicity/oncogenicity study of tributyl phosphate in the rat. Toxicology 128: 125-134 (1998b).

16 HOW SUPPLIED/STORAGE AND HANDLING

Octagam 5% liquid is supplied in 1.0 g, 2.5 g, 5 g, 10 g or 25 g single use bottles.

 | Octagam 5%
Carton NDC Number | Container NDC Number | Size | Grams Protein
0069-8400-02 | 0069-8400-01 | 20 mL | 1.0
0069-8425-02 | 0069-8425-01 | 50 mL | 2.5
0069-8451-02 | 0069-8451-01 | 100 mL | 5.0
0069-8476-02 | 0069-8476-01 | 200 mL | 10.0

- Octagam 5% liquid is not supplied with an infusion set. If a filtered infusion set is used (not mandatory), the filter size must be 0.2 – 200 microns.
- Components used in the packaging of Octagam 5% liquid are not made with natural rubber latex.
- Octagam 5% liquid may be stored for 36 months at +2°C to + 8°C (36°F to 46°F) from the date of manufacture. Within the first 24 months of this shelf life, the product may be stored at ≤ +25°C (77°F). After storage at ≤ +25°C (77°F) the product must be used or discarded.
- Do not use after expiration date.
- Do not freeze. Do not use product that has been frozen.
- Any unused product or waste material should be disposed of in accordance with local requirements.

17 PATIENT COUNSELING INFORMATION

Information for Patients

(See also Boxed Warning and Warnings and Precautions [ 5 ])

Inform patients of the early signs of hypersensitivity reactions including hives, generalized urticaria, tightness of the chest, wheezing, hypotension, and anaphylaxis. Instruct patients that they should contact their physicians immediately if such symptoms occur. (See Warnings and Precautions [ 5.1 ])

Instruct patients to immediately report the following signs and symptoms to their health care provider:

- symptoms of thrombosis which may include pain and/or swelling of an arm or leg with warmth over the affected area; discoloration of an arm or leg; unexplained shortness of breath; chest pain or discomfort that worsens on deep breathing; unexplained rapid pulse; numbness or weakness on one side of the body. (see Warnings and Precautions [ 5.5 ])
- decreased urine output, sudden weight gain, fluid retention/edema, and/or shortness of breath (see Warnings and Precautions [ 5.2 ])
- severe headache, neck stiffness, drowsiness, fever, sensitivity to light, painful eye movements, nausea, and vomiting (see Warnings and Precautions [ 5.6 ])
- fatigue, increased heart rate, yellowing of the skin or eyes, and dark-colored urine (see Warning and Precautions [ 5.7 ])
- trouble breathing, chest pain, blue lips or extremities, lightheadedness and fever These may be signs for TRALI which typically occurs within 1 to 6 hours following transfusion (see Warning and Precautions [ 5.8 ])

Inform patients that Octagam 5% liquid is made from human plasma and may contain infectious agents that can cause disease (e.g., viruses, and, theoretically, the CJD agent). Inform patients that the risk Octagam 5% liquid may transmit an infectious agent has been reduced by screening plasma donors for prior exposure to certain viruses, by testing the donated plasma for certain virus infections and by inactivating and/or removing certain viruses during manufacturing. Nevertheless, instruct patients that they should report any symptoms that concern them (see Warning and Precautions ([ 5.9 ]).

Inform patients that administration of IgG may interfere with the response to live viral vaccines such as measles, mumps and rubella. Inform patients to notify their immunizing physician of therapy with Octagam 5% liquid (see Drug Interactions [ 7 ]).

Manufactured by:

Octapharma Pharmazeutika Produktionsges.m.b.H.

Oberlaaer Strasse 235

A-1100 Vienna, Austria

Octapharma AB

Lars Forssells gata 23

SE- 112 75, Sweden

U.S License No. 1646

PACKAGE LABEL - PRINCIPAL DISPLAY PANEL

Immune Globulin Intravenous (Human), 5%

Octagam 5%

20 mL

NDC 0069-8400-02

Octagam 5%

50 mL

NDC 0069-8425-02

Octagam 5%

100 mL

NDC 0069-8451-02

Octagam 5%

200 mL

NDC 0069-8476-02